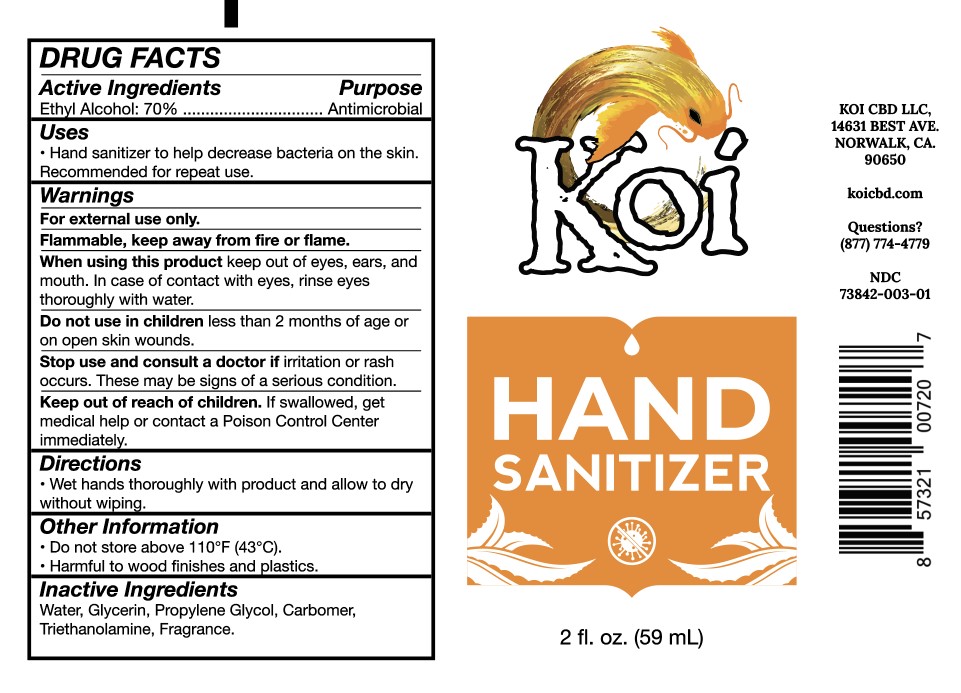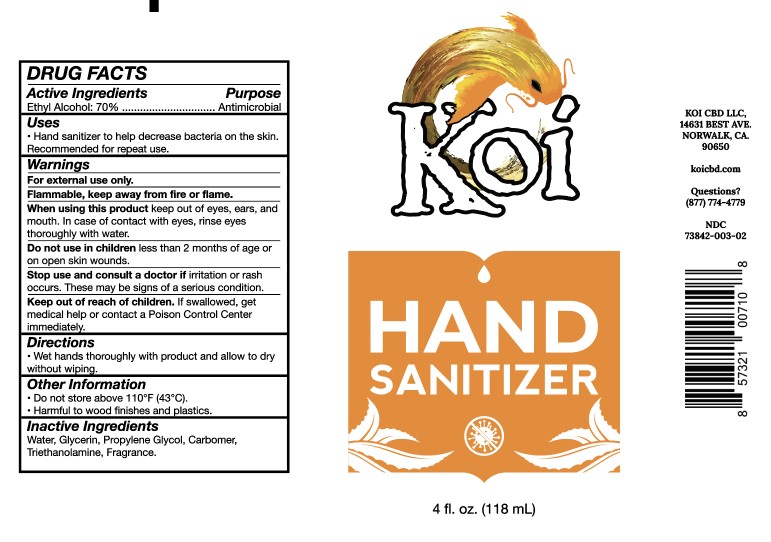 DRUG LABEL: Koi Hand Sanitizer
NDC: 73842-003 | Form: GEL
Manufacturer: Koi CBD LLC
Category: otc | Type: HUMAN OTC DRUG LABEL
Date: 20200803

ACTIVE INGREDIENTS: ALCOHOL 70 g/100 mL
INACTIVE INGREDIENTS: CARBOMER HOMOPOLYMER, UNSPECIFIED TYPE; PROPYLENE GLYCOL; TROLAMINE; WATER; GLYCERIN

Koi Hand Sanitizer

ACTIVE INGREDIENT

Ethyl Alcohol 70%...... Antimicrobial

PURPOSE

Antimicrobial

INDICATIONS AND USAGE

Hand sanitizer to help decrease bacteria on the skin. Recommended for repeat use.

WARNINGS

For external use only. Flammable, keep away from fire or flames.

Do not use in children less than 2 months of age or on open skin wounds.

Stop use and consult a doctor if irritation or rash occurs. These may be signs of a serious condition.

Keep out of reach of children. If swallowed, get medical help or contact a Poison Control Center immediately.

DOSAGE AND ADMINISTRATION

Wet hands thoroughly with product and allow to dry without wiping.

STORAGE AND HANDLING

Do not store about 110°F. Harmful to wood finishes and plastics.

INACTIVE INGREDIENT

Water, Glycerin, Propylene Glycol,Carbomer, Triethanolamine, Fragrance.

PACKAGE LABEL

NDC 73842-003-001 Bottle 59 mL

NDC 73842-003-002 Bottle 118 mL